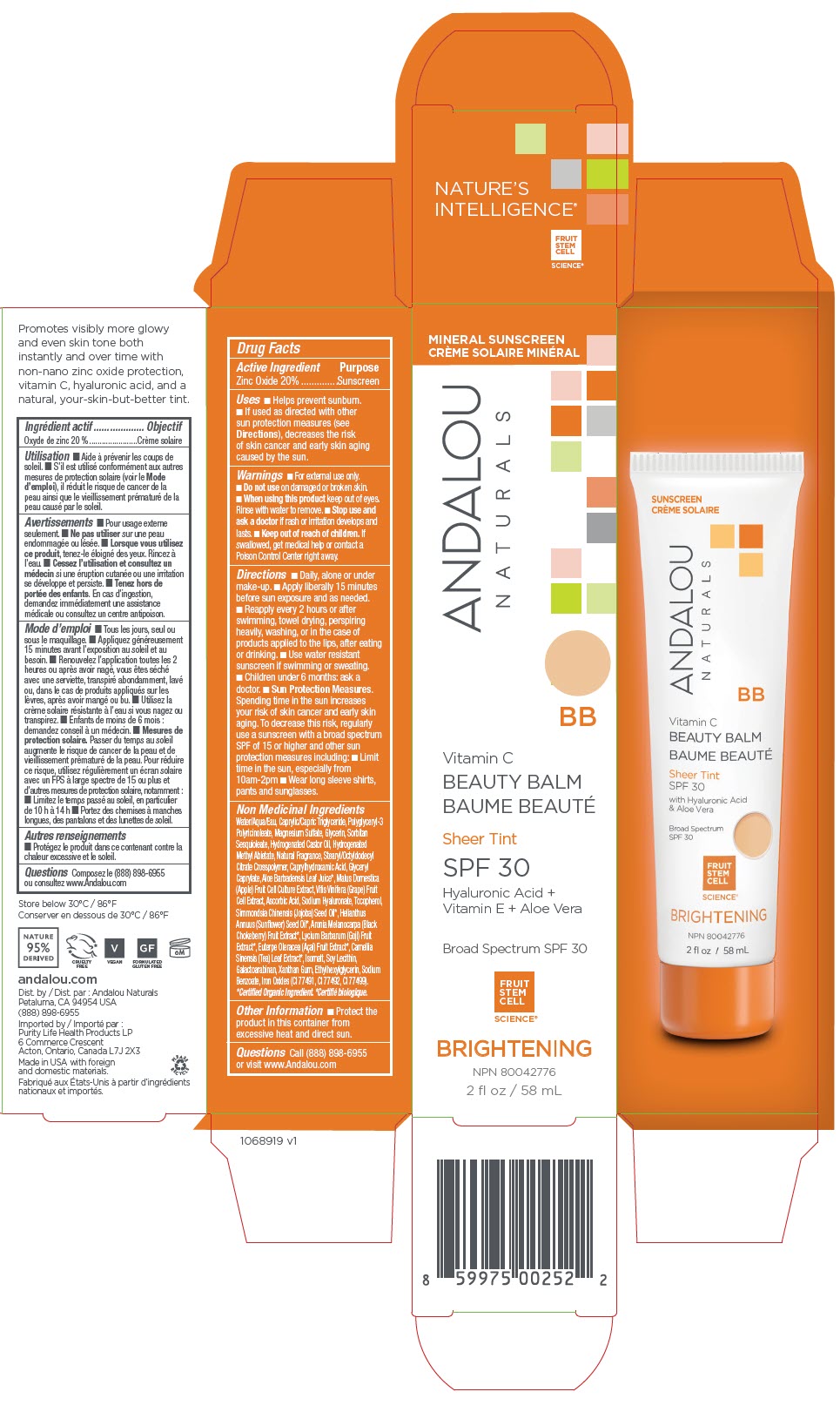 DRUG LABEL: Vitamin C BB Beauty Balm Sheer Tint SFP 30
NDC: 55560-0108 | Form: LOTION
Manufacturer: Andalou naturals
Category: otc | Type: HUMAN OTC DRUG LABEL
Date: 20250611

ACTIVE INGREDIENTS: ZINC OXIDE 200 mg/1 mL
INACTIVE INGREDIENTS: WATER; MEDIUM-CHAIN TRIGLYCERIDES; POLYGLYCERYL-3 PENTARICINOLEATE; MAGNESIUM SULFATE, UNSPECIFIED FORM; GLYCERIN; SORBITAN SESQUIOLEATE; HYDROGENATED CASTOR OIL; HYDROGENATED METHYL ABIETATE; STEARYL/OCTYLDODECYL CITRATE CROSSPOLYMER; CAPRYLHYDROXAMIC ACID; GLYCERYL MONOCAPRYLATE; ALOE VERA LEAF; APPLE; VITIS VINIFERA HIGH TANNIN CULTIVAR FRUIT CELL LYSATE; ASCORBIC ACID; HYALURONATE SODIUM; TOCOPHEROL; JOJOBA OIL; SUNFLOWER OIL; ARONIA MELANOCARPA FRUIT JUICE; LYCIUM BARBARUM FRUIT; ACAI; TEA LEAF; ISOMALT; SOYBEAN LECITHIN; GALACTOARABINAN; XANTHAN GUM; ETHYLHEXYLGLYCERIN; SODIUM BENZOATE; FERRIC OXIDE YELLOW; FERRIC OXIDE RED; FERROSOFERRIC OXIDE

Vitamin C BB Beauty Balm Sheer Tint SPF 30

Drug Facts

Active Ingredient

Zinc Oxide 20%

Purpose

Sunscreen

Uses

- Helps prevent sunburn.
- If used as directed with other sun protection measures (see Directions), decreases the risk of skin cancer and early skin aging caused by the sun.

Warnings

- For external use only.

- Do not use on damaged or broken skin.

- When using this product keep out of eyes. Rinse with water to remove.

- Stop use and ask a doctor if rash or irritation develops and lasts.

- Keep out of reach of children. If swallowed, get medical help or contact a Poison Control Center right away.

Directions

- Daily, alone or under make-up.
- Apply liberally 15 minutes before sun exposure and as needed.
- Reapply every 2 hours or after swimming, towel drying, perspiring heavily, washing, or in the case of products applied to the lips, after eating or drinking.
- Use water resistant sunscreen if swimming or sweating.
- Children under 6 months: ask a doctor.
- Sun Protection Measures. Spending time in the sun increases your risk of skin cancer and early skin aging. To decrease this risk, regularly use a sunscreen with a broad spectrum SPF of 15 or higher and other sun protection measures including:
  - Limit time in the sun, especially from 10am-2pm
  - Wear long sleeve shirts, pants and sunglasses.

Non Medicinal Ingredients

Water/Aqua/Eau, Caprylic/Capric Triglyceride, Polyglyceryl-3 Polyricinoleate, Magnesium Sulfate, Glycerin, Sorbitan Sesquioleate, Hydrogenated Castor Oil, Hydrogenated Methyl Abietate, Natural Fragrance, Stearyl/Octyldodecyl Citrate Crosspolymer, Caprylhydroxamic Acid, Glyceryl Caprylate, Aloe Barbadensis Leaf Juice [Certified Organic Ingredient.] , Malus Domestica (Apple) Fruit Cell Culture Extract, Vitis Vinifera (Grape) Fruit Cell Extract, Ascorbic Acid, Sodium Hyaluronate, Tocopherol, Simmondsia Chinensis (Jojoba) Seed Oil, Helianthus Annuus (Sunflower) Seed Oil, Aronia Melanocarpa (Black Chokeberry) Fruit Extract, Lycium Barbarum (Goji) Fruit Extract, Euterpe Oleracea (Açai) Fruit Extract, Camellia Sinensis (Tea) Leaf Extract, Isomalt, Soy Lecithin, Galactoarabinan, Xanthan Gum, Ethylhexylglycerin, Sodium Benzoate, Iron Oxides (CI 77491, CI 77492, CI 77499).

Other Information

- Protect the product in this container from excessive heat and direct sun.

Questions

Call (888) 898-6955 or visit www.Andalou.com

Dist. by: Andalou Naturals
Petaluma, CA 94954 USA

PRINCIPAL DISPLAY PANEL - 58 mL Tube Carton

MINERAL SUNSCREEN

ANDALOU
NATURALS

BB

Vitamin C
BEAUTY BALM

Sheer Tint
SPF 30
Hyaluronic Acid +
Vitamin E + Aloe Vera

Broad Spectrum SPF 30

FRUIT
STEM
CELL
SCIENCE®

BRIGHTENING
NPN 80042776
2 fl oz / 58 mL